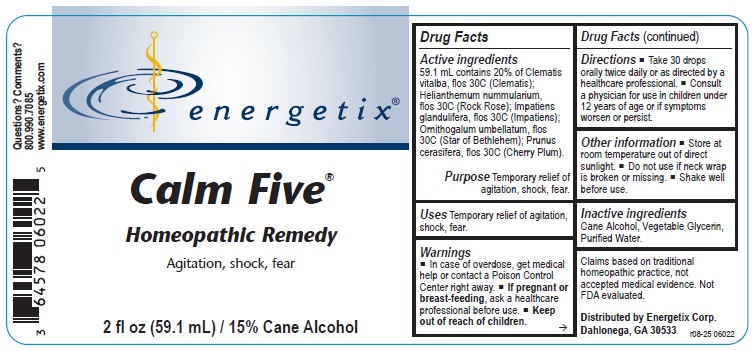 DRUG LABEL: Calm Five
NDC: 64578-0157 | Form: LIQUID
Manufacturer: Energetix Corporation
Category: homeopathic | Type: HUMAN OTC DRUG LABEL
Date: 20251217

ACTIVE INGREDIENTS: CLEMATIS VITALBA FLOWER 30 [hp_C]/59 mL; HELIANTHEMUM NUMMULARIUM FLOWER 30 [hp_C]/59 mL; IMPATIENS GLANDULIFERA FLOWER 30 [hp_C]/59 mL; ORNITHOGALUM UMBELLATUM 30 [hp_C]/59 mL; PRUNUS CERASIFERA FLOWER 30 [hp_C]/59 mL
INACTIVE INGREDIENTS: GLYCERIN; WATER; ALCOHOL

Calm Five

Active ingredients

59.1 mL contains 20% of Clematis vitalba, flos 30C (Clematis); Helianthemum nummularium, flos 30C (Rock Rose); Impatiens glandulifera, flos 30C (Impatiens); Ornithogalum umbellatum, flos 30C (Star of Bethlehem); Prunus cerasifera, flos 30C (Cherry Plum).

Claims based on traditional homeopathic practice, not accepted medical evidence. Not FDA evaluated.

Uses

Temporary relief of agitation, shock, fear.

Warnings

- In case of overdose, get medical help or contact a Poison Control Center right away.
- If pregnant or breast-feeding, ask a healthcare professional before use.

- Keep out of reach of children.

Directions

- Take 30 drops orally twice daily or as directed by a healthcare professional.
- Consult a physician for use in children under 12 years of age or if symptoms worsen or persist.

Other information

- Store at room temperature out of direct sunlight.
- Do not use if neck wrap is broken or missing.
- Shake well before use.

Inactive ingredients

Cane Alcohol, Vegetable Glycerin, Purified Water.

QUESTIONS

Distributed by Energetix Corp.
Dahlonega, GA 30533
Questions? Comments?
800.990.7085
www.energetix.com

PACKAGE LABEL

energetix

Calm Five

Homeopathic Remedy

Agitation, shock, fear

2 fl oz (59.1 mL) / 15% Cane Alcohol

PURPOSE

PurposeTemporary relief of agitation, shock, fear.